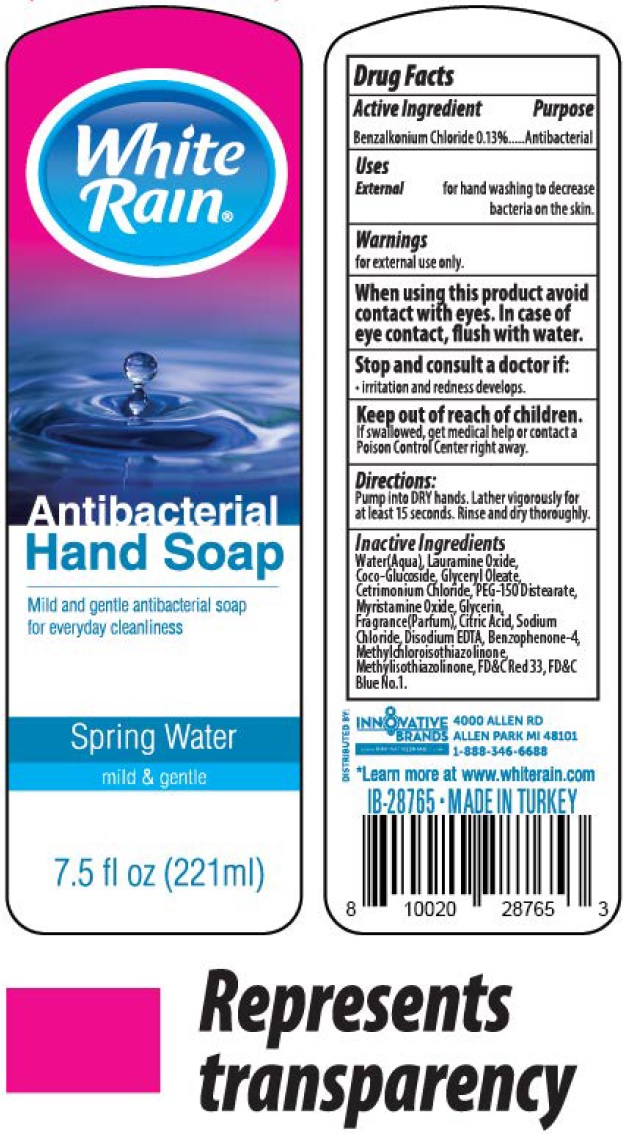 DRUG LABEL: White Rain Antibacterial Hand SPRING WATER
NDC: 52862-624 | Form: LIQUID
Manufacturer: International Wholesale, Inc.
Category: otc | Type: HUMAN OTC DRUG LABEL
Date: 20231116

ACTIVE INGREDIENTS: BENZALKONIUM CHLORIDE 1.3 mg/1 mL
INACTIVE INGREDIENTS: WATER; LAURAMINE OXIDE; COCO GLUCOSIDE; GLYCERYL OLEATE; CETRIMONIUM CHLORIDE; PEG-150 DISTEARATE; MYRISTAMINE OXIDE; GLYCERIN; CITRIC ACID MONOHYDRATE; SODIUM CHLORIDE; EDETATE DISODIUM ANHYDROUS; SULISOBENZONE; METHYLCHLOROISOTHIAZOLINONE; METHYLISOTHIAZOLINONE; FD&C BLUE NO. 1

White Rain Antibacterial Hand Soap SPRING WATER

Active Ingredient

Benzalkonium Chloride 0.13%

Purpose

Antibacterial

Uses

for hand washing to decrease bacteria on the skin. External

Warnings

for external use only.

When using this product

avoid contact with eyes. In case of eye contact, flush with water.

Stop and consult a doctor if:

- irritation and redness develops.

Keep out of reach of children.

If swallowed, get medical help or contact a Poison Control Center right away.

Directions:

Pump into DRY hands, Lather vigorously for at least 15 seconds. Rinse and dry thoroughly.

Inactive Ingredients

Water(Aqua), Lauramine Oxide, Coco-Glucoside, Glyceryl Oleate, Cetrimonium Chloride, PEG-150 Distearate, Myristamine Oxide, Glycerin, Fragrance(Parfum), Citric Acid, Sodium Chloride, Disodium EDTA, Benzophenone-4, Methylchloroisothiazolinone, Methylisothiazolinone, FD&C Red 33, FD&C Blue No. 1.